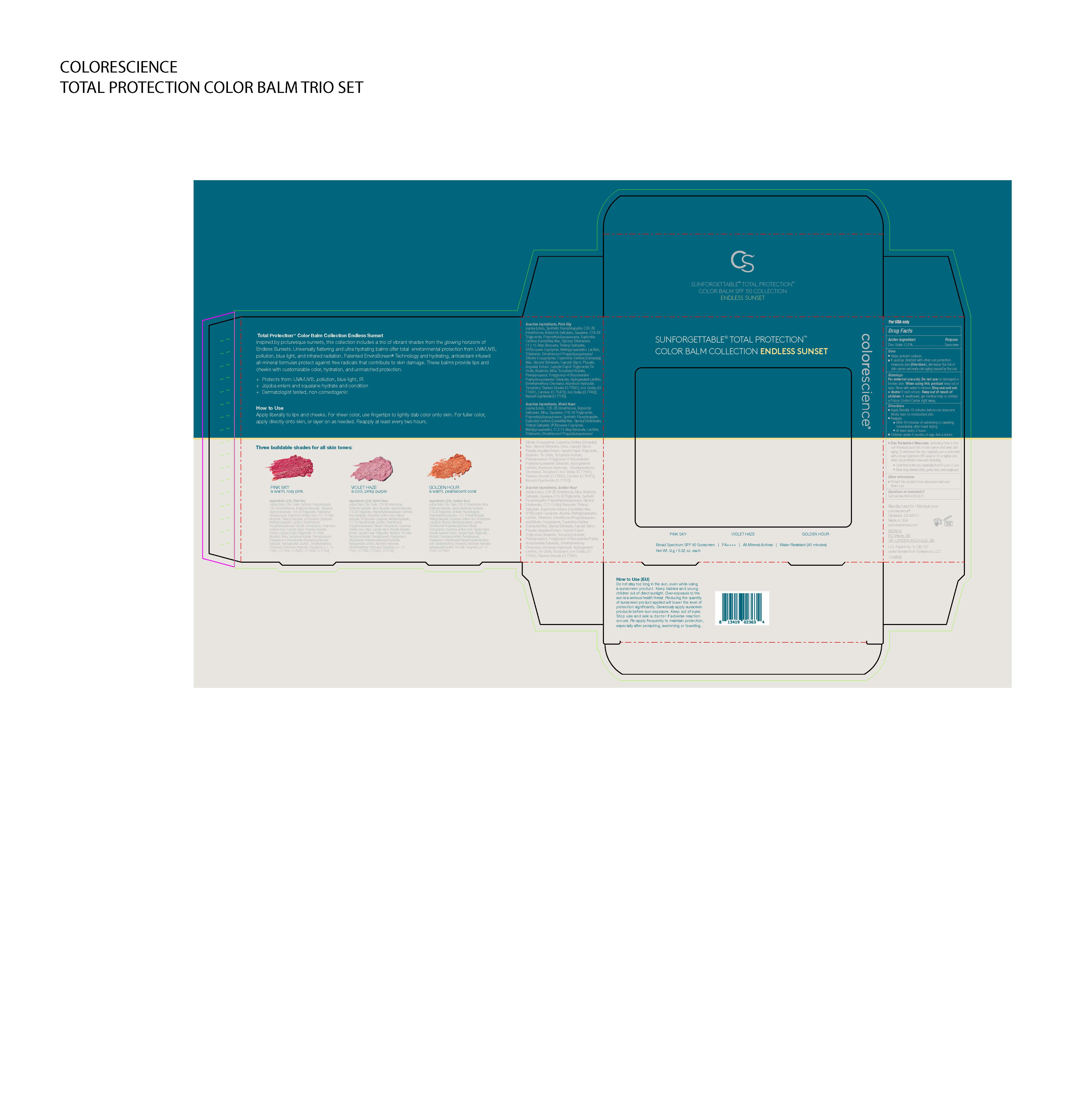 DRUG LABEL: SUNFORGETTABLE TOTAL PROTECTION COLOR BALM COLLECTION ENDLESSS ENDLESS SUNSET
NDC: 68078-065 | Form: STICK
Manufacturer: Colorescience
Category: otc | Type: HUMAN OTC DRUG LABEL
Date: 20251015

ACTIVE INGREDIENTS: ZINC OXIDE 125 mg/1 g
INACTIVE INGREDIENTS: FERRIC OXIDE RED; HYDROLYZED JOJOBA ESTERS (ACID FORM); GLYCERYL BEHENATE/EICOSADIOATE; MICA; TOCOPHEROL; DIMETHICONE; CARNAUBA WAX; POLYMETHYLSILSESQUIOXANE (4.5 MICRONS); DIMETHYLMETHOXY CHROMANOL; TRIDECYL SALICYLATE; LECITHIN, SOYBEAN; SQUALANE; BUTYLOCTYL SALICYLATE; TITANIUM DIOXIDE; CAPRYLYL GLYCOL; METHYLPROPANEDIOL; PHENYLPROPANOL; C18-36 ACID TRIGLYCERIDE; .ALPHA.-BISABOLOL, (+/-)-; ALUMINUM HYDROXIDE; POLYGLYCERYL-4 DIISOSTEARATE/POLYHYDROXYSTEARATE/SEBACATE; STANNOUS OXIDE; ALKYL (C12-15) BENZOATE; CANDELILLA WAX; DIMETHICONOL/PROPYLSILSESQUIOXANE/SILICATE CROSSPOLYMER (450000000 MW)

SUNFORGETTABLE TOTAL PROTECTION COLOR BALM COLLECTION ENDLESSS ENDLESS SUNSET